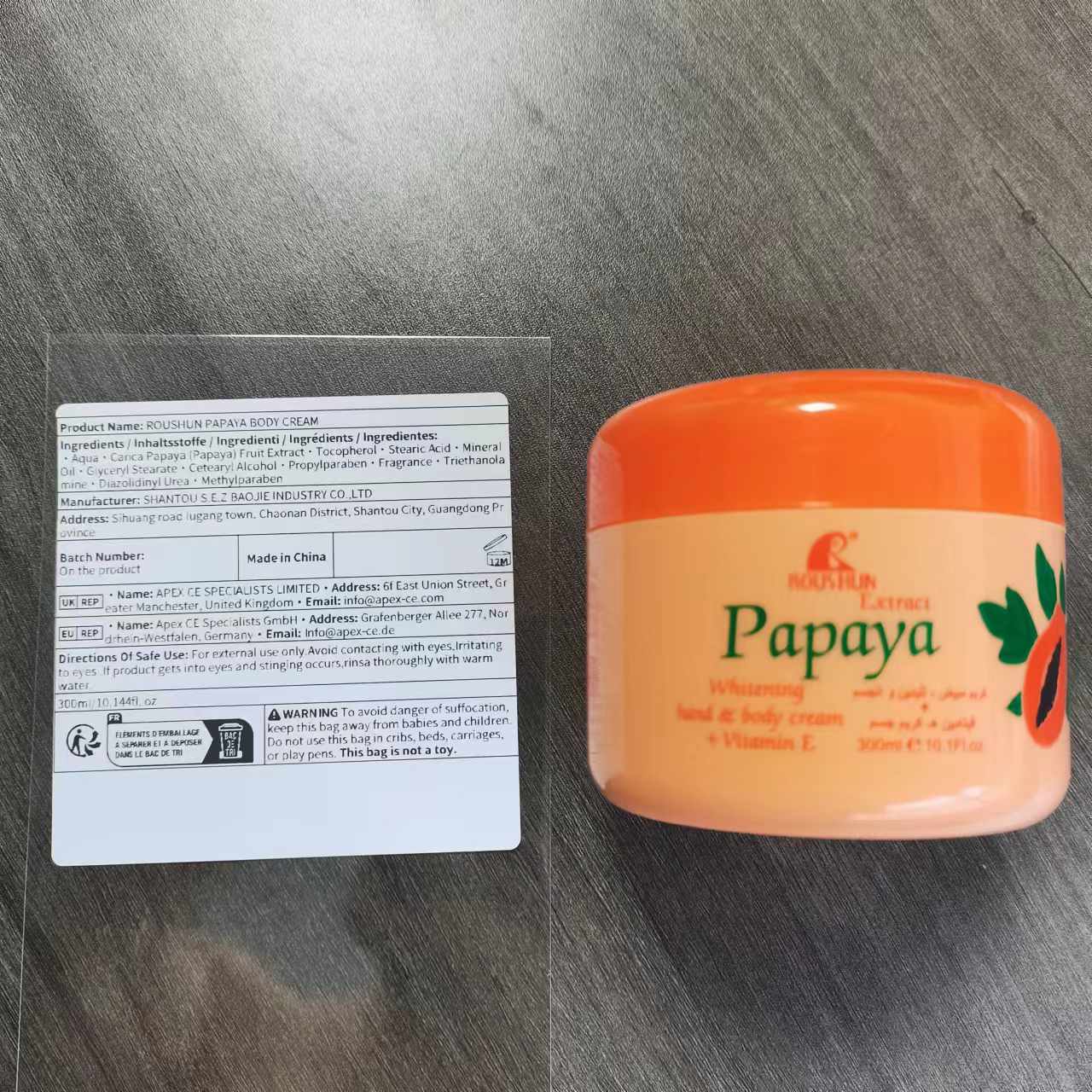 DRUG LABEL: Q7 Carrot Body
NDC: 84551-012 | Form: LOTION
Manufacturer: Kunshan Julian Trading Co., Ltd.
Category: otc | Type: HUMAN OTC DRUG LABEL
Date: 20241012

ACTIVE INGREDIENTS: TOCOPHEROL 2.5 g/100 g
INACTIVE INGREDIENTS: WATER 83.5 g/100 g

ACTIVE INGREDIENT

Tocopherol 2.5%

STEARIC ACID 3%

MINERAL OIL 3%

Carica Papaya (Papaya) Fruit Extract 5%

PURPOSE

whitening

USAGE

If used daily, it can enhance the skin's whitening and moisturizing effects, making the skin appear more fair and radiant.

KEEP OUT OF REACH OF CHILDREN

If swallowed,get medical help or contact a Poison Control Center right away.

DO NOT USE

on damaged or broken skin.

Stop use and ask a doctor if

rash occurs

When using this product

keep out of eyes.rinse with water to remove.

WARNINGS

For extermal use only

DOSAGE & ADMINSTRATION

BID, 5-10g per dose
Ext.

Inactive ingredient section

water